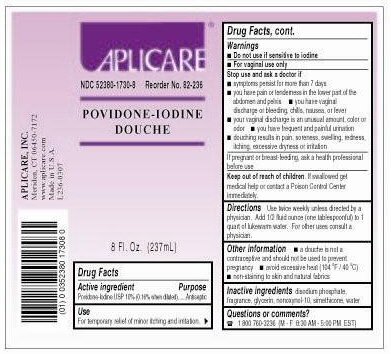 DRUG LABEL: Aplicare Povidone-iodine 
NDC: 52380-1730 | Form: DOUCHE
Manufacturer: Aplicare, Inc.
Category: otc | Type: HUMAN OTC DRUG LABEL
Date: 20100426

ACTIVE INGREDIENTS: Povidone-iodine 10 g/100 g
INACTIVE INGREDIENTS: Nonoxynol-10; Glycerin; Dimethicone; Silicon Dioxide; Sodium Phosphate, Dibasic Anhydrous; Water

Drug Facts

ACTIVE INGREDIENT

Povidone-Iodine USP 10% (0.16% when diluted)

PURPOSE

Antiseptic

For temporary relief of minor itching and irritation

Do not use if sensitive to iodine

For vaginal use only

Stop use and ask a doctor if

- symptoms persist for more than 7 days you have pain or tenderness in the lower part of the
  abdomen and pelvis
- you have vaginal discharge or bleeding, chills, nausea, or fever
- your vaginal discharge is an unusual amount, color or odor
- you have frequent and painful urination
- douching results in pain, soreness, swelling, redness,itching, excessive dryness or irritation

ASK DOCTOR

If pregnant or breast-feeding, ask a health professional before use

DOSAGE AND ADMINISTRATION

Use twice weekly unless directed by a physician. Add 1/2 fluid ounce (one tablespoonful) to 1 quart of lukewarm water. For other uses consult a physician.

Questions or comments?

1 800 760-3236 (M-F 8:30 AM - 5:00 PM EST)

PACKAGE LABEL

Povidone-iodine Douche